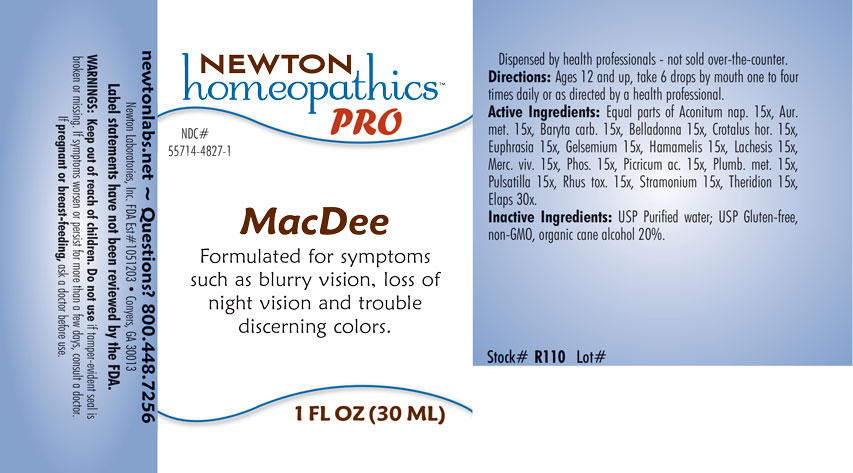 DRUG LABEL: MacDee
NDC: 55714-4827 | Form: LIQUID
Manufacturer: Newton Laboratories, Inc.
Category: homeopathic | Type: HUMAN OTC DRUG LABEL
Date: 20201204

ACTIVE INGREDIENTS: ACONITUM NAPELLUS 15 [hp_X]/1 mL; BARIUM CARBONATE 15 [hp_X]/1 mL; ATROPA BELLADONNA 15 [hp_X]/1 mL; CROTALUS HORRIDUS HORRIDUS VENOM 15 [hp_X]/1 mL; EUPHRASIA STRICTA 15 [hp_X]/1 mL; GELSEMIUM SEMPERVIRENS ROOT 15 [hp_X]/1 mL; HAMAMELIS VIRGINIANA ROOT BARK/STEM BARK 15 [hp_X]/1 mL; LACHESIS MUTA VENOM 15 [hp_X]/1 mL; MERCURY 15 [hp_X]/1 mL; PHOSPHORUS 15 [hp_X]/1 mL; PICRIC ACID 15 [hp_X]/1 mL; LEAD 15 [hp_X]/1 mL; ANEMONE PULSATILLA 15 [hp_X]/1 mL; TOXICODENDRON PUBESCENS LEAF 15 [hp_X]/1 mL; DATURA STRAMONIUM 15 [hp_X]/1 mL; THERIDION CURASSAVICUM 15 [hp_X]/1 mL; MICRURUS CORALLINUS VENOM 30 [hp_X]/1 mL; GOLD 15 [hp_X]/1 mL
INACTIVE INGREDIENTS: WATER; ALCOHOL

MacDee 4827L

INDICATIONS & USAGE SECTION

Formulated for symptoms such as blurry vision, loss of night vision and trouble discerning colors.

DOSAGE & ADMINISTRATION SECTION

Directions: Ages 12 and up, take 6 drops by mouth one to four times daily or as directed by a health professional.

OTC - ACTIVE INGREDIENT SECTION

Equal parts of Aconitum napellus 15x, Aurum metallicum 15x, Baryta carbonica 15x, Belladonna 15x, Crotalus horridus 15x, Euphrasia officinalis 15x, Gelsemium sempervirens 15x, Hamamelis virginiana 15x, Lachesis mutus 15x, Mercurius vivus 15x, Phosphorus 15x, Picricum acidum 15x, Plumbum metallicum 15x, Pulsatilla 15x, Rhus toxicodendron 15x, Stramonium 15x, Theridion 15x, Elaps corallinus 30x.

OTC - PURPOSE SECTION

Formulated for symptoms such as blurry vision, loss of night vision and trouble discerning colors.

INACTIVE INGREDIENT SECTION

Inactive Ingredients: USP Purified Water; USP Gluten-free, non-GMO, organic cane alcohol 20%.

QUESTIONS SECTION

newtonlabs.net - Questions? 800.448.7256

Newton Laboratories, Inc. FDA Est # 1051203 Conyers, GA 30013

WARNINGS SECTION

WARNINGS: Keep out of reach of children. Do not use if tamper-evident seal is broken or missing. If symptoms worsen or persist for more than a few days, consult a doctor. If pregnant or breast-feeding, ask a doctor before use.

OTC - PREGNANCY OR BREAST FEEDING SECTION

If pregnant or breast-feeding, ask a doctor before use.

OTC - KEEP OUT OF REACH OF CHILDREN SECTION

Keep out of reach of children.